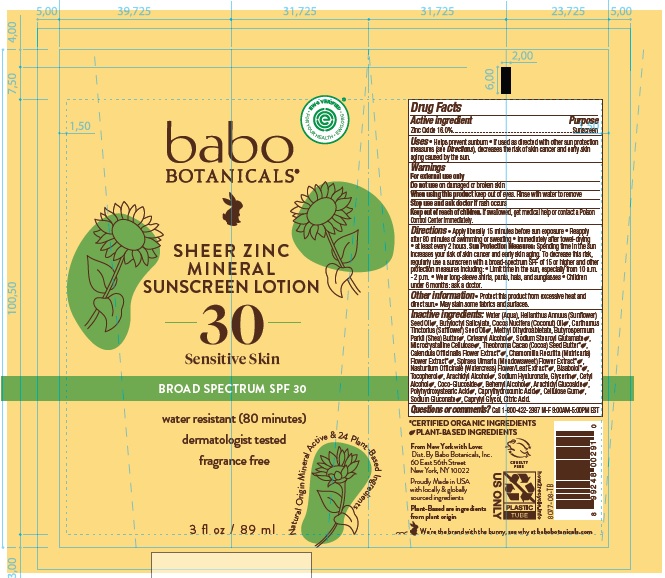 DRUG LABEL: Babo Botanicals Sheer Zinc Mineral Sunscreen SPF30
NDC: 79265-7708 | Form: LOTION
Manufacturer: Babo Botanicals, Inc.
Category: otc | Type: HUMAN OTC DRUG LABEL
Date: 20251009

ACTIVE INGREDIENTS: ZINC OXIDE 160 mg/1 mL
INACTIVE INGREDIENTS: WATER; COCONUT OIL; SUNFLOWER OIL; HYALURONATE SODIUM; CETOSTEARYL ALCOHOL; ARACHIDYL GLUCOSIDE; ARACHIDYL ALCOHOL; POLYHYDROXYSTEARIC ACID (2300 MW); METHYL DIHYDROABIETATE; NASTURTIUM OFFICINALE FLOWERING TOP; CALENDULA OFFICINALIS FLOWER; CHAMOMILE; CITRIC ACID MONOHYDRATE; SODIUM STEAROYL GLUTAMATE; CARBOXYMETHYLCELLULOSE SODIUM, UNSPECIFIED FORM; COCOA BUTTER; DOCOSANOL; LEVOMENOL; FILIPENDULA ULMARIA FLOWER; TOCOPHEROL; CELLULOSE, MICROCRYSTALLINE; SODIUM GLUCONATE; SHEA BUTTER; CAPRYLHYDROXAMIC ACID; CAPRYLYL GLYCOL; SAFFLOWER OIL; BUTYLOCTYL SALICYLATE; CETYL ALCOHOL; COCO GLUCOSIDE; GLYCERIN

Babo Botanicals Sheer Zinc Mineral Sunscreen SPF30

Active ingredient

Zinc Oxide 16.0%

Purpose

Sunscreen

Uses

- Helps prevent sunburn.
- If used as directed with other sun protection measures (see Directions), decreases the risk of skin cancer and early skin aging caused by the sun.

Warnings

For external use only

Do not use

on damaged or broken skin

When using this product

keep out of eyes. Rinse with water to remove

Stop use and ask doctor if

rash occurs

Keep out of reach of children.

If swallowed, get medical help or contact a Poison Control Center immediately.

Directions

- Apply liberally 15 minutes before sun exposure
- Reapply after 80 minutes of swimming or sweating
- immediately after towel-drying
- at least every 2 hours.

Sun Protection Measures: Spending time in the sun increases your risk of skin cancer and early skin aging. To decrease this risk,

regularly use a sunscreen with a broad-spectrum SPF of 15 or higher and other protection measures including:

- Limit time in the sun, especially from 10 a.m. - 2 p.m.
- Wear long-sleeve shirts, pants, hats, and sunglasses
- Children under 6 months: ask a doctor.

Other information

- Protect this product from excessive heat and direct sun
- May stain some fabrics and surfaces.

Inactive ingredients

Water (Aqua), Helianthus Annuus (Sunflower) Seed Oil, Butyloctyl Salicylate, Cocos Nucifera (Coconut) Oil, CarthamusTinctorius (Safflower) Seed Oil, Methyl Dihydroabietate, Butyrospermum Parkii (Shea) Butter, Cetearyl Alcohol, Sodium Stearoyl Glutamate, Microcrystalline Cellulose, Theobroma Cacao (Cocoa) Seed Butter*, Calendula Officinalis Flower Extract*, Chamomilla Recutita (Matricaria) Flower Extract*, Spiraea Ulmaria (Meadowsweet) Flower Extract*, Nasturtium Officinale (Watercress) Flower/Leaf Extract*, Bisabolol*, Tocopherol, Arachidyl Alcohol, Sodium Hyaluronate, Glycerin, Cetyl Alcohol, Coco-Glucoside, Behenyl Alcohol, Arachidyl Glucoside, Polyhydroxystearic Acid, Caprylhydroxamic Acid, Cellulose Gum, Sodium Gluconate, Caprylyl Glycol, Citric Acid.

*Certified Organic Ingredients

Questions or comments?

Call 1-800-422-2987 M-F 9:00AM - 5:00PM EST